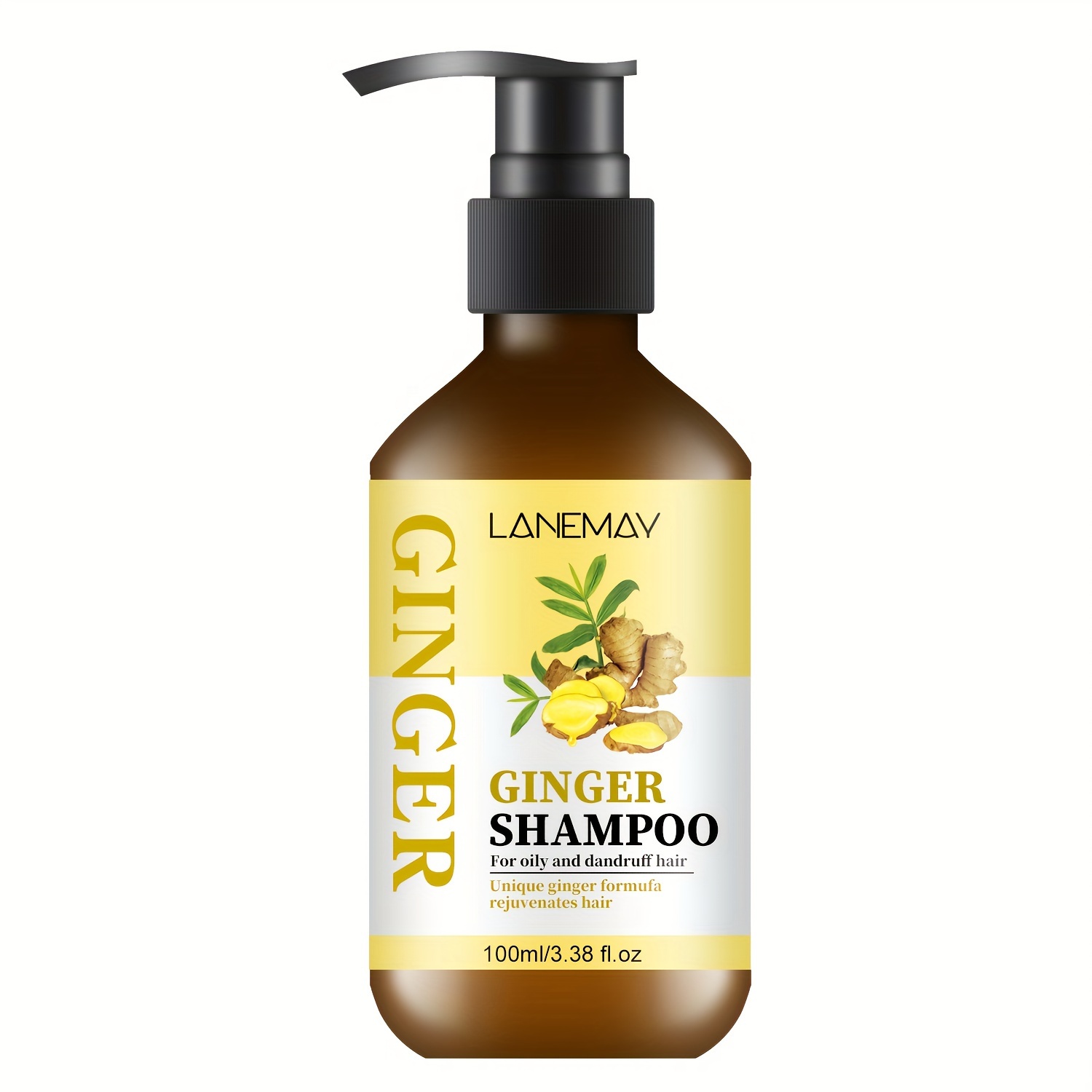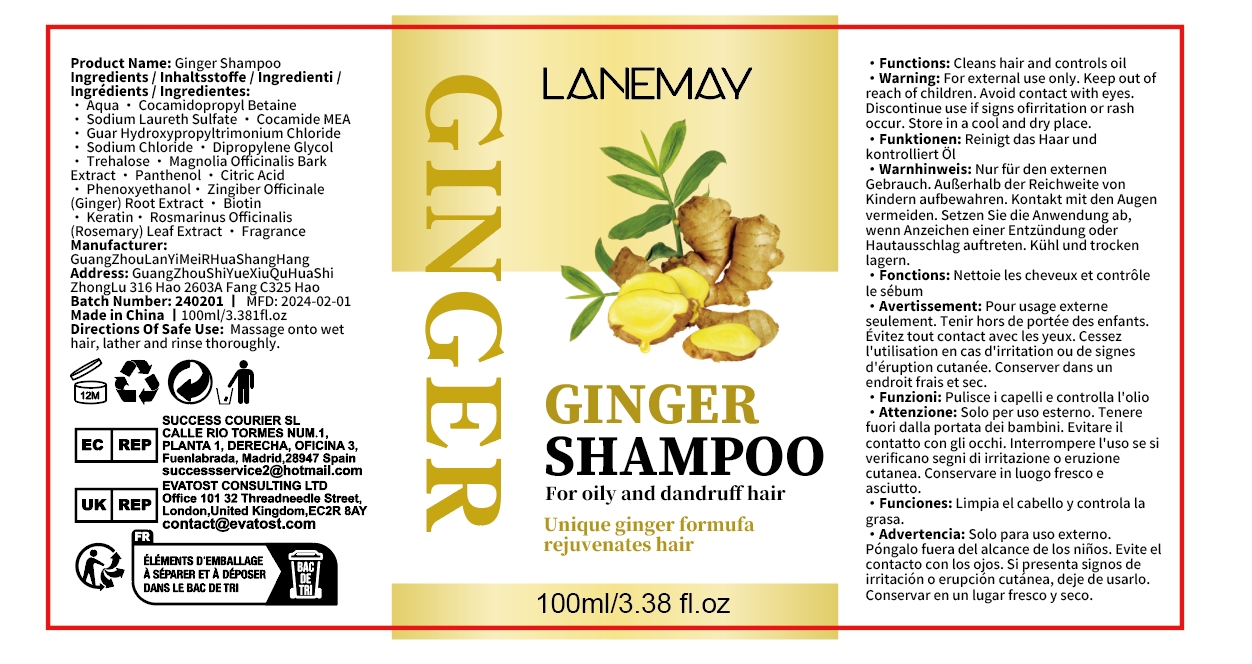 DRUG LABEL: GingerShampoo
NDC: 84025-030 | Form: SHAMPOO
Manufacturer: Guangzhou Yanxi Biotechnology Co., Ltd
Category: otc | Type: HUMAN OTC DRUG LABEL
Date: 20240406

ACTIVE INGREDIENTS: COCAMIDOPROPYL BETAINE 5 mg/100 mL
INACTIVE INGREDIENTS: WATER

DOSAGE AND ADMINISTRATION

As a normal cleaning shampoo

INDICATIONS AND USAGE

Massage onto wet hair, lather and rinse thoroughly.

WARNINGS

For external use only.

INACTIVE INGREDIENT

Aqua

Keep out of reach of children.

PURPOSE

Cleans hair and controls oil